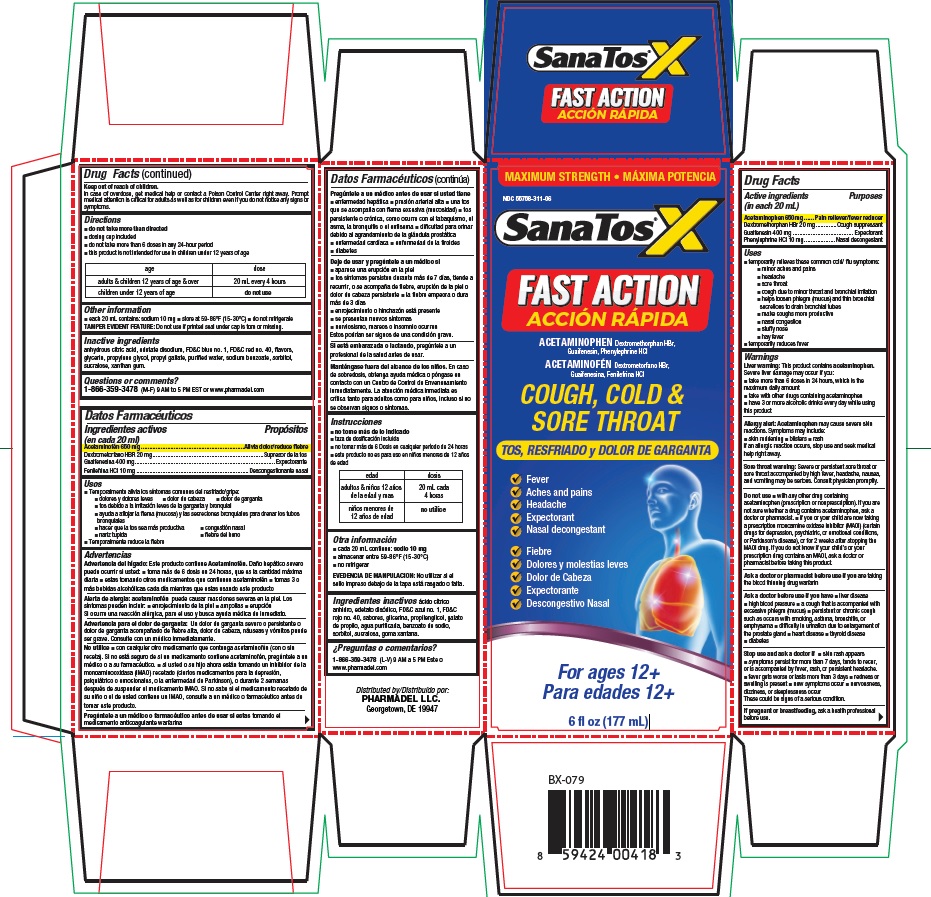 DRUG LABEL: SanaTos X
NDC: 55758-311 | Form: LIQUID
Manufacturer: Pharmadel LLC
Category: otc | Type: HUMAN OTC DRUG LABEL
Date: 20231114

ACTIVE INGREDIENTS: DEXTROMETHORPHAN HYDROBROMIDE 20 mg/1 1; ACETAMINOPHEN 650 mg/1 1; GUAIFENESIN 400 mg/1 1; PHENYLEPHRINE HYDROCHLORIDE 10 mg/1 1
INACTIVE INGREDIENTS: ANHYDROUS CITRIC ACID; EDETATE DISODIUM; FD&C BLUE NO. 1; PROPYLENE GLYCOL; PROPYL GALLATE; SORBITOL; SUCRALOSE; XANTHAN GUM; WATER; FD&C RED NO. 40; GLYCERIN; SODIUM BENZOATE

SanaTos X Fast Action (PLE)(APTA)

Active ingredients and Purposes

PURPOSE

Active ingredients (in each 20 mL) | Purposes
Acetaminophen 650mg ...... | Pain reliever/fever reducer
Dextromethorphan HBr 20 mg ............. | Cough suppressant
Guaifenesin 400 mg ..................................... | Expectorant
Phenylephrine HCI 10 mg................... | Nasal decongestant

Uses

- temporarily relieves these common cold/ flu symptoms:
- minor aches and pains
- headache
- sore throat
- cough due to minor throat and bronchial irritation
- helps loosen phlegm (mucus) and thin bronchial
- secretions to drain bronchial tubes
- make coughs more productive
- nasal congestion
- stuffy nose
- hay fever
- temporarily reduces fever

Warnings

Liver warning:

This product contains acetaminophen.
Severe liver damage may occur if you:

- take more than 6 doses in 24 hours, which is the maximum daily amount
- take with other drugs containing acetaminophen
- have 3 or more alcoholic drinks every day while using this product

Allergy alert:

Acetaminophen may cause severe skin reactions. Symptoms may include:

- skin reddening
- blisters
- rash If an allergic reaction occurs, stop use and seek medical help right away.

Sore throat warning:

Severe or persistent sore throat or sore throat accompanied by high fever, headache, nausea, and vomiting may be serious. Consult physician promptly.

Do not use

- with any other drug containing acetaminophen (prescription or nonprescription). If you are not sure whether a drug contains acetaminophen, ask a doctor or pharmacist.
- if you or your child are now taking a prescription monoamine oxidase inhibitor (MAOI) (certain drugs for depression, psychiatric, or emotional conditions, or Parkinson's disease), or for 2 weeks after stopping the MAOI drug. If you do not know if your child’s or your prescription drug contains an MAOI, ask a doctor or pharmacist before taking this product.

Ask a doctor or pharmacist before use if you are

taking the blood thinning drug warfarin

Ask a doctor before use if you have

- liver disease
- high blood pressure
- a cough that is accompanied with excessive phlegm (mucus)
- persistent or chronic cough such as occurs with smoking, asthma, bronchitis, or emphysema
- diffculty in urination due to enlargement of the prostate gland
- heart disease
- thyroid disease
- diabetes

Stop use and ask a doctor if

- skin rash appears
- symptoms persist for more than 7 days, tends to recur, or is accompanied by fever, rash, or persistent headache.
- fever gets worse or lasts more than 3 days
- redness or swelling is present
- new symptoms occur
- nervousness, dizziness, or sleeplessness occur

These could be signs of a serious condition.

If pregnant or breastfeeding,

ask a health professional before use.

Keep out of reach of children.

In case of overdose, get medical help or contact a Poison Control Center right away. Prompt medical attention is critical for adults as well as for children even if you do not notice any signs or symptoms.

Directions

- do not take more than directed
- dosing cup included
- do not take more than 6 doses in any 24-hour period
- this product is not intended for use in children under 12 years of age

age | dose
adults & children 12 years of age & over | 20 mL every 4 hours
children under 12 years of age | do not use

Other information

- each 20 mL contains: sodium 10 mg
- store at 59-86°F (15-30°C)
- do not refrigerate

TAMPER EVIDENT FEATURE: Do not use if printed seal under cap is torn or missing.

Inactive ingredients

anhydrous citric acid, edetate disodium, FD&C blue no. 1, FD&C red no. 40, flavors, glycerin, propylene glycol, propyl gallate, purified water, sodium benzoate, sorbitol, sucralose, xanthan gum.

Questions or comments?

1-866-359-3478 (M-F) 9 AM to 5 PM EST or www.pharmadel.com

Principal Display Panel

MAXIMUM STRENGTH • MÁXIMA POTENCIA

SANATOS® X

FAST ACTION/ACCIÓN RÁPIDA

ACETAMINOPHEN Dextromethorphan HBr, Guaifenesin, Phenylephrine HCI/ACETAMINOFÉN Dextrometorfano HBr,
Guaifenesina, Fenilefrina HCl

COUGH, COLD & SORE THROAT/TOS, RESFRIADO y DOLOR DE GARGANTA

Fever/Fiebre
Aches and pains/Dolores y molestias leves
Headache/Dolor de Cabeza
Expectorant/Expectorante
Nasal decongestant/Descongestivo Nasal

For ages 12+/Para edades 12+

6 fl oz (177 mL)